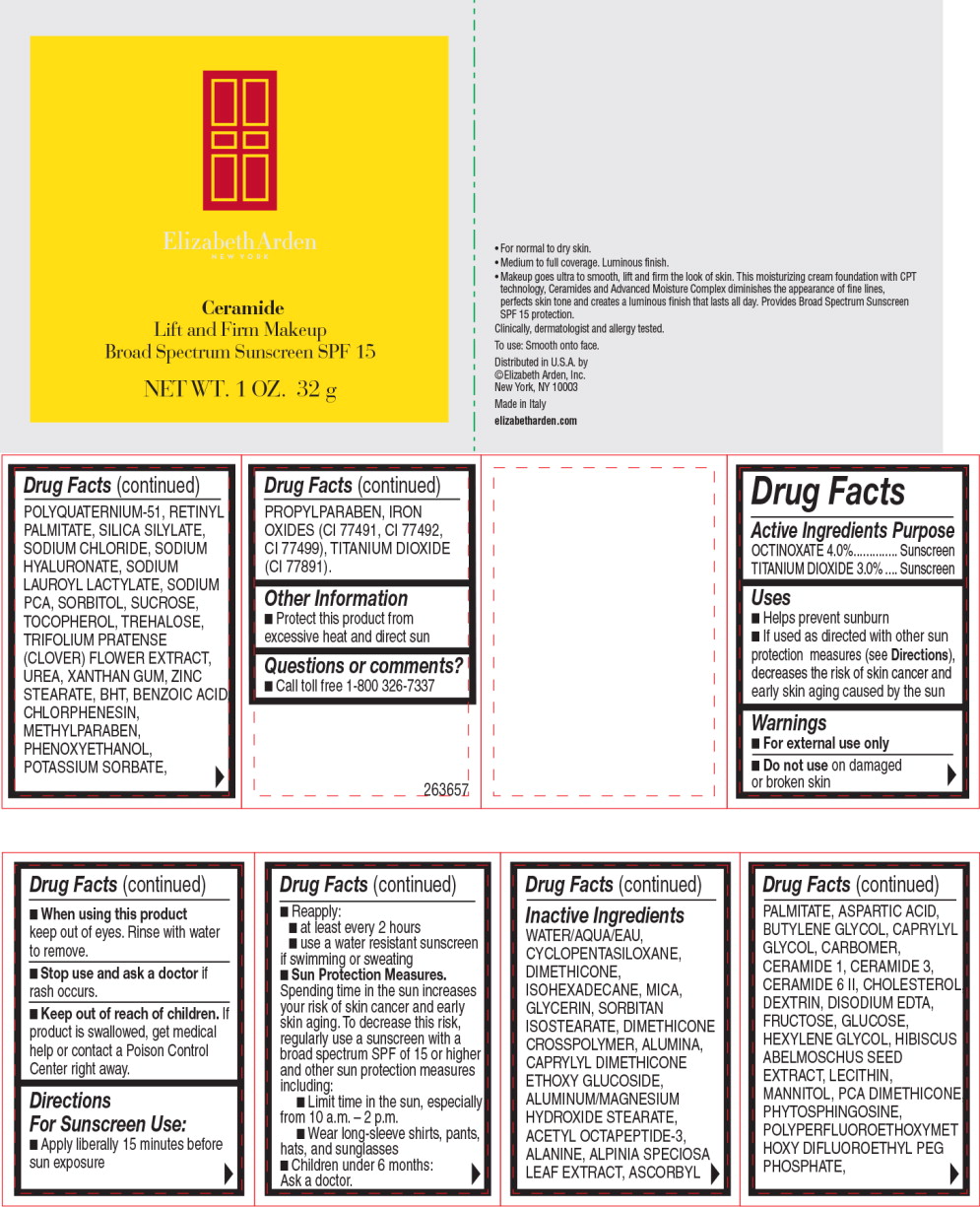 DRUG LABEL: CERAMIDE LIFT AND FIRM MAKEUP BROAD SPECTRUM SUNSCREEN SPF 15 CAMEO
NDC: 67938-0942 | Form: CREAM
Manufacturer: ELIZABETH ARDEN, INC
Category: otc | Type: HUMAN OTC DRUG LABEL
Date: 20150716

ACTIVE INGREDIENTS: OCTINOXATE 1.28 g/32 g; TITANIUM DIOXIDE .96 g/32 g
INACTIVE INGREDIENTS: ACETYL OCTAPEPTIDE-3; ALANINE; ALPINIA ZERUMBET LEAF; ALUMINUM OXIDE; ASCORBYL PALMITATE; ASPARTIC ACID; BENZOIC ACID; BUTYLATED HYDROXYTOLUENE; BUTYLENE GLYCOL; CAPRYLYL GLYCOL; CERAMIDE 1; CERAMIDE 3; CERAMIDE 6 II; CHLORPHENESIN; CHOLESTEROL; CYCLOMETHICONE 5; ICODEXTRIN; DIMETHICONE; EDETATE DISODIUM; FRUCTOSE; DEXTROSE, UNSPECIFIED FORM; GLYCERIN; HEXYLENE GLYCOL; ABELMOSCHUS MOSCHATUS SEED; FERROSOFERRIC OXIDE; FERRIC OXIDE RED; FERRIC OXIDE YELLOW; ISOHEXADECANE; MANNITOL; METHYLPARABEN; MICA; PHENOXYETHANOL; PHYTOSPHINGOSINE; POTASSIUM SORBATE; PROPYLPARABEN; VITAMIN A PALMITATE; SODIUM CHLORIDE; HYALURONATE SODIUM; SODIUM LAUROYL LACTYLATE; SODIUM PYRROLIDONE CARBOXYLATE; SORBITAN ISOSTEARATE; SORBITOL; SUCROSE; TOCOPHEROL; TREHALOSE; TRIFOLIUM PRATENSE FLOWER; UREA; WATER; XANTHAN GUM; ZINC STEARATE

Drug Facts

Active ingredients

OCTINOXATE 4.0%

TITANIUM DIOXIDE 3.0%

Purpose

Sunscreen

Sunscreen

Uses

- Helps prevent sunburn
- If used as directed with other sun protection measures (see Directions), decreases the risk of skin cancer and early skin aging caused by the sun

Warnings

- For external use only

- Do not use on damaged or broken skin

- When using this product keep out of eyes. Rinse with water to remove.

- Stop use and ask a doctor if rash occurs.

- Keep out of reach of children. If product is swallowed, get medical help or contact a Poison Control Center right away.

Directions For Sunscreen Use:

- Apply liberally 15 minutes before sun exposure
- Reapply:
  - at least every 2 hours
  - use a water resistant sunscreen if swimming or sweating
- Sun Protection Measures. Spending time in the sun increases your risk of skin cancer and early skin aging. To decrease this risk, regularly use a sunscreen with a broad spectrum SPF of 15 or higher and other sun protection measures including:
  - Limit time in the sun, especially from 10 a.m. - 2 p.m.
  - Wear long-sleeve shirts, pants, hats, and sunglasses
- Children under 6 months: Ask a doctor.

Inactive Ingredients

WATER/AQUA/EAU, CYCLOPENTASILOXANE, DIMETHICONE, ISOHEXADECANE, MICA, GLYCERIN, SORBITAN ISOSTEARATE, DIMETHICONE CROSSPOLYMER, ALUMINA, CAPRYLYL DIMETHICONE ETHOXY GLUCOSIDE, ALUMINUM/MAGNESIUM HYDROXIDE STEARATE, ACETYL OCTAPEPTIDE-3, ALANINE, ALPINIA SPECIOSA LEAF EXTRACT, ASCORBYL PALMITATE, ASPARTIC ACID, BUTYLENE GLYCOL, CAPRYLYL GLYCOL, CARBOMER, CERAMIDE 1, CERAMIDE 3, CERAMIDE 6 II, CHOLESTEROL DEXTRIN, DISODIUM EDTA, FRUCTOSE, GLUCOSE, HEXYLENE GLYCOL, HIBISCUS ABELMOSCHUS SEED EXTRACT, LECITHIN, MANNITOL, PCA DIMETHICONE PHYTOSPHINGOSINE, POLYPERFLUOROETHOXYMET HOXY DIFLUOROETHYL PEG PHOSPHATE, POLYQUATERNIUM-51, RETINYL PALMITATE, SILICA SILYLATE, SODIUM CHLORIDE, SODIUM HYALURONATE, SODIUM LAUROYL LACTYLATE, SODIUM PCA, SORBITOL, SUCROSE, TOCOPHEROL, TREHALOSE, TRIFOLIUM PRATENSE (CLOVER) FLOWER EXTRACT UREA, XANTHAN GUM, ZINC STEARATE, BHT, BENZOIC ACID CHLORPHENESIN, METHYLPARABEN, PHENOXYETHANOL, POTASSIUM SORBATE, PROPYLPARABEN, IRON OXIDES (CI 77491, CI 77492, CI 77499), TITANIUM DIOXIDE (CI 77891).

Other Information

- Protect this product from excessive heat and direct sun

Questions or comments?

- Call toll free 1-800 326-7337

Principal Display Panel - Carton Label

Elizabeth Arden

NEW YORK

Ceramide

Lift and Firm Makeup

Broad Spectrum Sunscreen SPF 15

NET WT. 1 OZ. 32 g